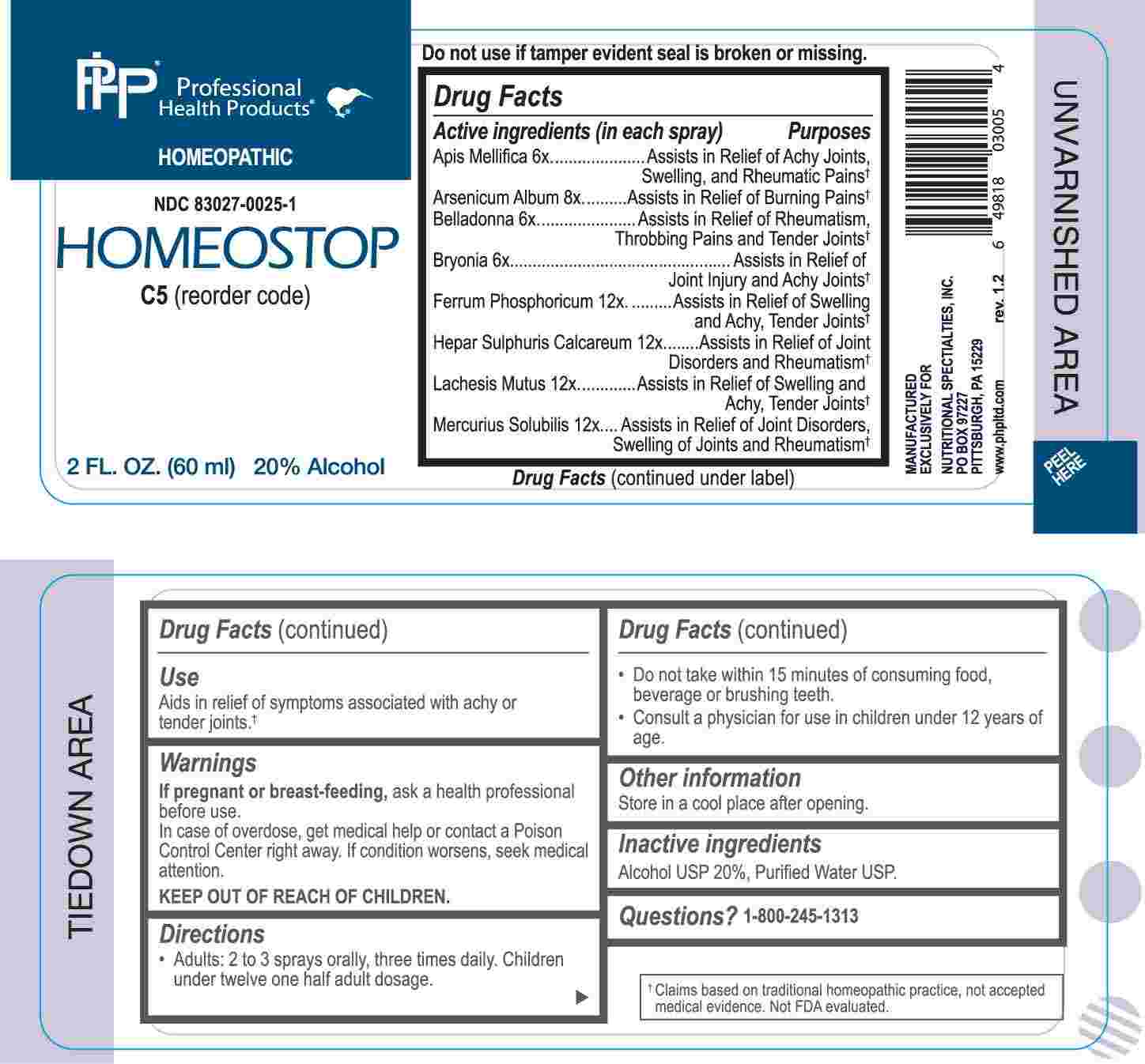 DRUG LABEL: Homeostop
NDC: 83027-0025 | Form: SPRAY
Manufacturer: Nutritional Specialties, Inc.
Category: homeopathic | Type: HUMAN OTC DRUG LABEL
Date: 20250401

ACTIVE INGREDIENTS: APIS MELLIFERA 6 [hp_X]/1 mL; ATROPA BELLADONNA 6 [hp_X]/1 mL; BRYONIA ALBA ROOT 6 [hp_X]/1 mL; ARSENIC TRIOXIDE 8 [hp_X]/1 mL; FERROSOFERRIC PHOSPHATE 12 [hp_X]/1 mL; CALCIUM SULFIDE 12 [hp_X]/1 mL; LACHESIS MUTA VENOM 12 [hp_X]/1 mL; MERCURIUS SOLUBILIS 12 [hp_X]/1 mL
INACTIVE INGREDIENTS: WATER; ALCOHOL

DRUG FACTS:

ACTIVE INGREDIENTS:

Apis Mellifica 6X, Arsenicum Album 8X, Belladonna 6X, Bryonia 6X, Ferrum Phosphoricum 12X, Hepar Sulphuris Calcareum 12X, Lachesis Mutus 12X, Mercurius Solubilis 12X.

PURPOSE:

Apis Mellifica – Assists in Relief of Achy Joints, Swelling, and Rheumatic Pains,† Arsenicum Album – Assists in Relief of Buring Pains,† Belladonna – Assists in Relief of Rheumatism, Throbbing Pains and Tender Joints,† Bryonia – Assists in Relief of Joint Injury and Achy Joints,† Ferrum Phosphoricum – Assists in Relief of Swelling and Achy, Tender Joints,† Hepar Sulphuris Calcareum – Assists in Relief of Joint Disorders and Rheumatism,† Lachesis Mutus – Assists in Relief of Swelling and Achy, Tender Joints,† Mercurius Solubilis – Assists in Relief of Joint Disorders, Swelling of Joints and Rheumatism†

†Claims based on traditional homeopathic practice, not accepted medical evidence. Not FDA evaluated.

USES:

Aids in relief of symptoms associated with achy or tender joints.†

†Claims based on traditional homeopathic practice, not accepted medical evidence. Not FDA evaluated.

WARNINGS:

If pregnant or breast-feeding, ask a health professional before use.

In case of overdose, get medical help or contact a Poison Control Center right away.

If condition worsens, seek medical attention.

KEEP OUT OF REACH OF CHILDREN

Do not use if tamper evident seal is broken or missing.

Store in a cool place after opening

KEEP OUT OF REACH OF CHILDREN:

In case of overdose, get medical help or contact a Poison Control Center right away.

DIRECTIONS:

• Adults: 2 to 3 sprays orally, three times daily. Children under twelve one half adult dosage.

• Do not take within 15 minutes of consuming food, beverage or brushing teeth.

Consult a physician for use in children under 12 years of age.

INACTIVE INGREDIENTS:

Alcohol USP 20%, Purified Water USP.

QUESTIONS:

MANUFACTURED EXCLUSIVELY FOR

NUTRITIONAL SPECIALTIES, INC.

PO BOX 97227

PITTSBURG, PA 15229

www.phpltd.com

1-800-245-1313

PACKAGE LABEL DISPLAY:

Professional

Health Products

HOMEOPATHIC

NDC 83027-0025-1

HOMEOSTOP

2 FL. OZ (60 ml)